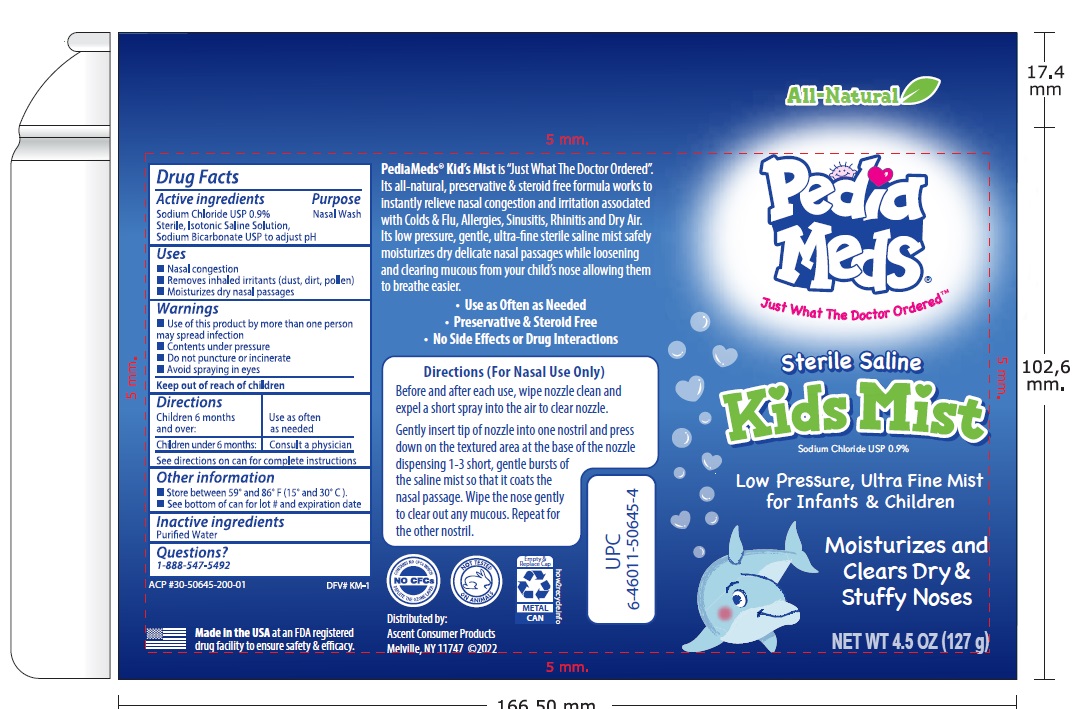 DRUG LABEL: Sterile Saline Kids Mist
NDC: 42829-003 | Form: SPRAY
Manufacturer: ASCENT CONSUMER PRODUCTS, INC.
Category: otc | Type: HUMAN OTC DRUG LABEL
Date: 20220808

ACTIVE INGREDIENTS: SODIUM CHLORIDE 0.9 g/100 g
INACTIVE INGREDIENTS: WATER

PediaMeds Sterile Saline Kids Mist

Active Ingredient

Sodium Chloride 0.9%

Sterile, Hypertonic Saline Solution,

Sodium Bicarbonate to adjust pH

Purpose

Nasal Wash

Uses

- Nasal congestion
- Removes inhaled irritants (dust, dirt, pollen)
- Moisturizes dry nasal passages

Directions

Children 6 months and over: Use as often as needed
Children under 6 months: Consult a physician

Warnings

Use of this product by more than one person may spread infection
Contents under pressure
Do not puncture or incinerate
Avoid spraying in eyes

Other Information

Store between 59 and 86 degree F

Inactive ingredients

Purfied Water

QUESTIONS ?

1-888-547-5492